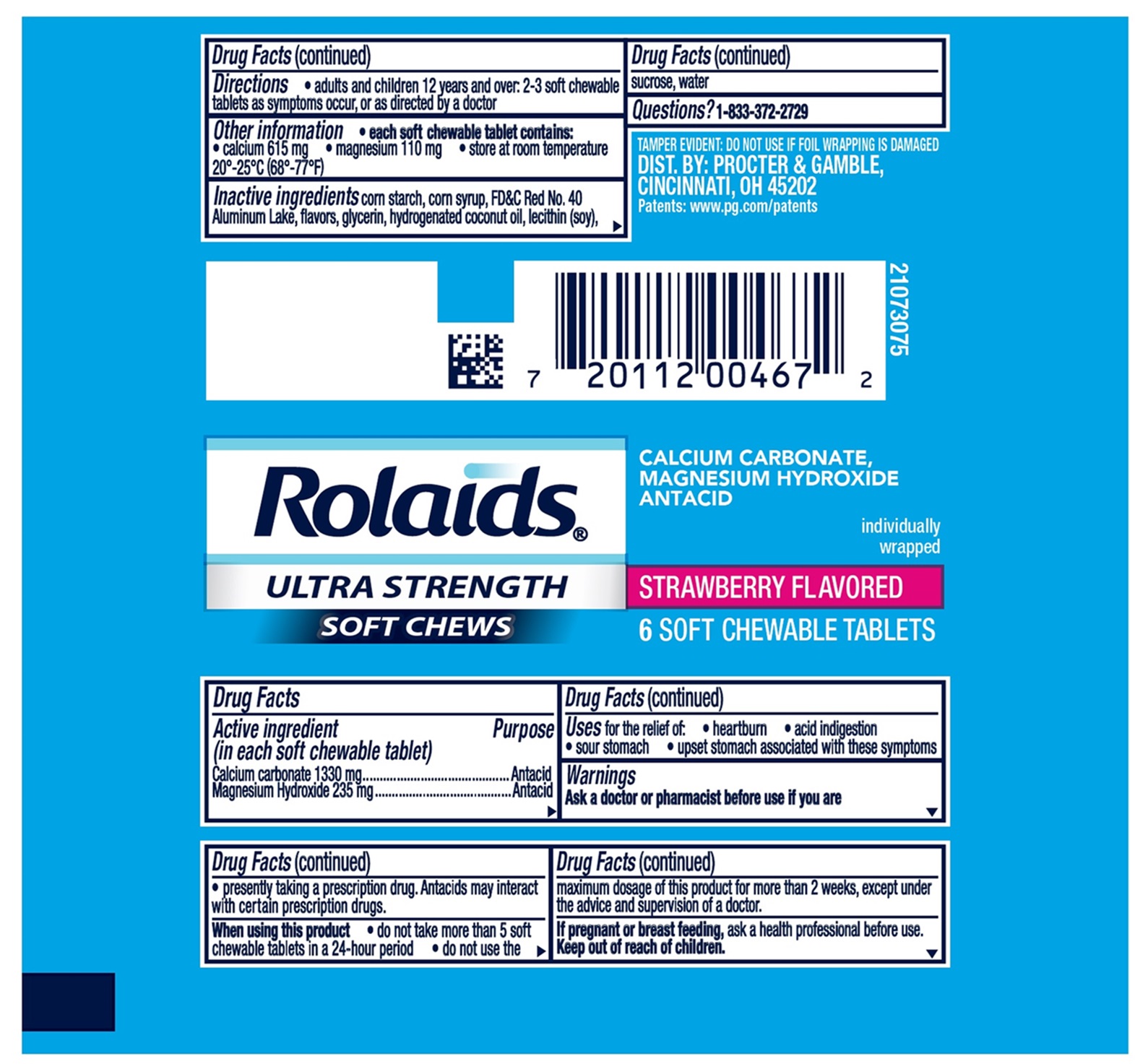 DRUG LABEL: Rolaids Ultra Strength Antacid
NDC: 69423-829 | Form: TABLET, CHEWABLE
Manufacturer: THE PROCTER & GAMBLE MANUFACTURING COMPANY
Category: otc | Type: HUMAN OTC DRUG LABEL
Date: 20251003

ACTIVE INGREDIENTS: CALCIUM CARBONATE 1330 mg/1 1; MAGNESIUM HYDROXIDE 235 mg/1 1
INACTIVE INGREDIENTS: FD&C RED NO. 40 ALUMINUM LAKE; STARCH, CORN; CORN SYRUP; GLYCERIN; HYDROGENATED COCONUT OIL; SUCROSE; WATER; LECITHIN, SOYBEAN

Rolaids® ULTRA STRENGTH SOFT CHEWS

Drug Facts

Active ingredients

(in each soft chewable tablet)
Calcium carbonate USP 1330 mg
Magnesium Hydroxide USP 235 mg

Purpose

Antacid
Antacid

Uses

for the relief of:

- heartburn
- acid indigestion
- sour stomach
- upset stomach associated with these symptoms

Warnings

Ask a doctor or pharmacist before use if you are

- presently taking a prescription drug. Antacids may interact with certain prescription drugs.

When using this product

- do not take more than 5 soft chewable tablets in a 24-hour period
- do not use the maximum dosage for more than 2 weeks, except under the advice and supervision of a doctor.

If pregnant or breastfeeding,

ask a health professional before use.

Directions

- adults and children 12 years and over: 2-3 soft chewable tablets as symptoms occur, or as directed by a doctor

Other information

- each soft chewable tablet contains: calcium 615 mg, magnesium 110 mg
- store at room temperature 20°-25°C (68°-77°F).

Inactive ingredients

corn starch, corn syrup, FD&C Red No 40 aluminum lake, flavors, glycerin, hydrogenated coconut oil, lecithin (soy), sucrose, water

Questions?

1-833-372-2729

DIST. BY: PROCTER & GAMBLE,

CINCINNATI, OH 45202

TAMPER EVIDENT: DO NOT USE IF FOIL WRAPPING IS DAMAGED.

PRINCIPAL DISPLAY PANEL

Rolaids

ULTRA STRENGTH

SOFT CHEWS

CALCIUM CARBONATE

MAGNESIUM HYDROXIDE

ANTACID

individually wrapped

STRAWBERRY FLAVORED

6 SOFT CHEWABLE TABLETS